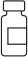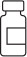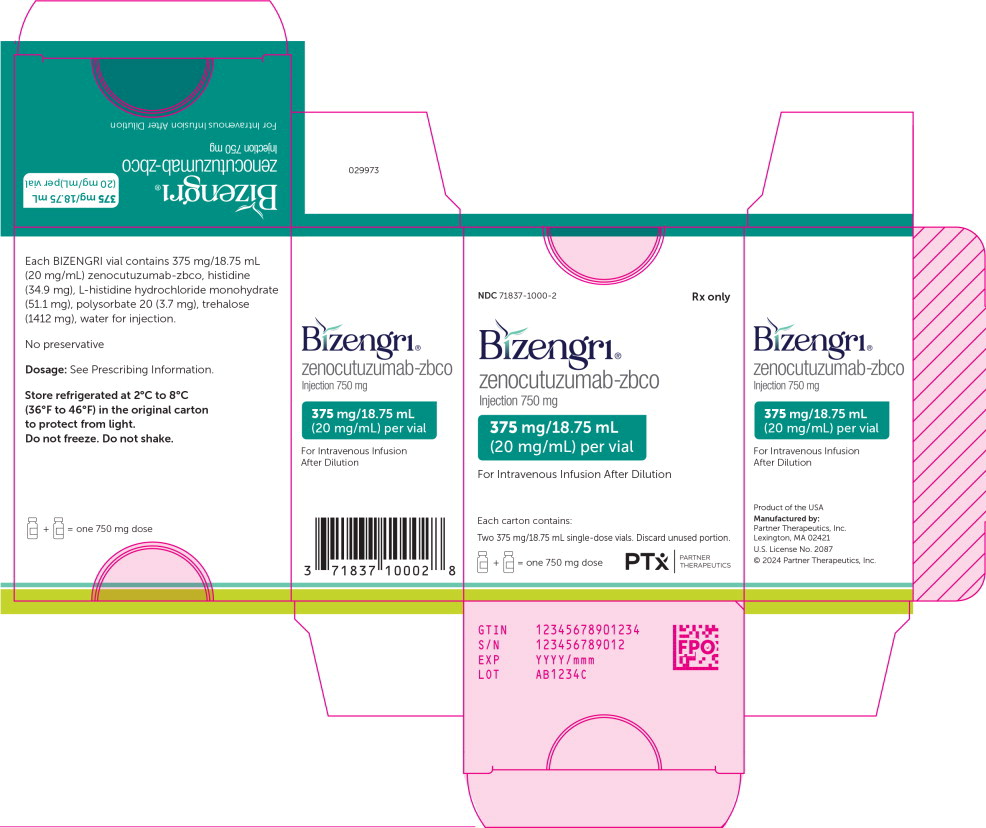 DRUG LABEL: BIZENGRI
NDC: 71837-1000 | Form: INJECTION
Manufacturer: Partner Therapeutics, Inc.
Category: prescription | Type: HUMAN PRESCRIPTION DRUG LABEL
Date: 20250307

ACTIVE INGREDIENTS: Zenocutuzumab 20 mg/1 mL
INACTIVE INGREDIENTS: histidine monohydrochloride monohydrate; histidine; trehalose dihydrate; polysorbate 20; water

HIGHLIGHTS OF PRESCRIBING INFORMATION

These highlights do not include all the information needed to use BIZENGRI® safely and effectively. See full prescribing information for BIZENGRI.
BIZENGRI (zenocutuzumab-zbco) injection, for intravenous use
Initial U.S. Approval: 2024

WARNING: EMBRYO-FETAL TOXICITY

See full prescribing information for complete boxed warning.

Embryo-Fetal Toxicity: Exposure to BIZENGRI during pregnancy can cause embryo-fetal harm. Advise patients of this risk and the need for effective contraception [see Warnings and Precautions (5.4), Use on Specific Populations (8.1, 8.3)].

1 INDICATIONS AND USAGE

BIZENGRI® is a bispecific HER2- and HER3-directed antibody indicated for the treatment of:

- Adults with advanced, unresectable or metastatic non-small cell lung cancer (NSCLC) harboring a neuregulin 1 (NRG1) gene fusion with disease progression on or after prior systemic therapy.* (1.1)
- Adults with advanced, unresectable or metastatic pancreatic adenocarcinoma harboring a neuregulin 1 (NRG1) gene fusion with disease progression on or after prior systemic therapy.* (1.2)

*This indication is approved under accelerated approval based on overall response rate and duration of response. Continued approval for this indication may be contingent upon verification and description of clinical benefit in a confirmatory trial(s).

2 DOSAGE AND ADMINISTRATION

- Select patients for treatment with BIZENGRI based on the presence of an NRG1 gene fusion. (2.1)
- Evaluate left ventricular ejection fraction (LVEF) before initiating BIZENGRI. (2.2)
- The recommended dosage of BIZENGRI is 750 mg every 2 weeks until disease progression or unacceptable toxicity. (2.3)
- Administer premedications before each infusion to reduce the risk of infusion-related reactions. (2.4)
- Administer as an intravenous infusion, after dilution, over 4 hours. (2.7)

3 DOSAGE FORMS AND STRENGTHS

Injection: 375 mg/18.75 mL (20 mg/mL) in a single-dose vial. (3)

4 CONTRAINDICATIONS

None. (4)

5 WARNINGS AND PRECAUTIONS

- Infusion-Related Reactions (IRR)/Hypersensitivity/Anaphylactic Reactions: Administer BIZENGRI in a setting with emergency resuscitation equipment and staff who are trained to monitor for IRRs and to administer emergency medications. Monitor for signs and symptoms of IRR. Interrupt infusion in patients with ≤ Grade 3 IRRs and administer symptomatic treatment as needed. Resume infusion at a reduced rate after resolution of symptoms. Immediately stop the infusion and permanently discontinue BIZENGRI for Grade 4 or life-threatening IRR or hypersensitivity/anaphylaxis. (5.1)
- Interstitial Lung Disease (ILD)/Pneumonitis: Monitor for new or worsening pulmonary symptoms indicative of ILD/pneumonitis. Permanently discontinue BIZENGRI in patients with ≥ Grade 2 ILD/pneumonitis. (5.2)
- Left Ventricular Dysfunction: Assess LVEF before initiating BIZENGRI and at regular intervals during treatment as clinically indicated. Manage through treatment interruption or discontinuation. Permanently discontinue BIZENGRI in patients with symptomatic congestive heart failure (CHF). (5.3)

6 ADVERSE REACTIONS

- The most common adverse reactions (≥ 10%) in patients were diarrhea musculoskeletal pain, fatigue, nausea, infusion-related reactions (IRR), dyspnea, rash, constipation, vomiting, abdominal pain, and edema. (6.1)
- The most common Grade 3 or 4 laboratory abnormalities (≥ 2%) were increased GGT, decreased hemoglobin, decreased sodium, decreased platelets, increased AST, increased ALT, increased alkaline phosphatase, decreased magnesium, decreased phosphate, increased aPTT and increased bilirubin. (6.1)

To report SUSPECTED ADVERSE REACTIONS, contact Partner Therapeutics, Inc. at 1-888-479-5385 or FDA at 1-800-FDA-1088 or www.fda.gov/medwatch.

8 USE IN SPECIFIC POPULATIONS

Females and Males of Reproductive Potential: Verify pregnancy status of females prior to initiation of BIZENGRI. (8.3)

FULL PRESCRIBING INFORMATION

WARNING: EMBRYO-FETAL TOXICITY

Embryo-Fetal Toxicity: Exposure to BIZENGRI during pregnancy can cause embryo-fetal harm. Advise patients of this risk and the need for effective contraception [see Warnings and Precautions (5.4), Use in Specific Populations (8.1, 8.3)].

1 INDICATIONS AND USAGE

1.1 Advanced Unresectable or Metastatic NRG1 Fusion-Positive Non-Small Cell Lung Cancer

BIZENGRI is indicated for the treatment of adults with advanced unresectable or metastatic non-small cell lung cancer (NSCLC) harboring a neuregulin 1 (NRG1) gene fusion with disease progression on or after prior systemic therapy.

This indication is approved under accelerated approval based on overall response rate and duration of response [see Clinical Studies (14.1)]. Continued approval for this indication may be contingent upon verification and description of clinical benefit in a confirmatory trial(s).

1.2 Advanced Unresectable or Metastatic NRG1 Fusion-Positive Pancreatic Adenocarcinoma

BIZENGRI is indicated for the treatment of adults with advanced unresectable or metastatic pancreatic adenocarcinoma harboring a neuregulin 1 (NRG1) gene fusion with disease progression on or after prior systemic therapy.

This indication is approved under accelerated approval based on overall response rate and duration of response [see Clinical Studies (14.2)]. Continued approval for this indication may be contingent upon verification and description of clinical benefit in a confirmatory trial(s).

2 DOSAGE AND ADMINISTRATION

2.1 Patient Selection

Select patients for treatment with BIZENGRI based on the presence of an NRG1 gene fusion in tumor specimens [see Clinical Studies (14.1, 14.2)].

An FDA-approved test for the detection of NRG1 gene fusions is not currently available.

2.2 Recommended Evaluation Before Initiating BIZENGRI

Before initiating BIZENGRI, evaluate left ventricular ejection fraction (LVEF) [see Warnings and Precautions (5.3)].

2.3 Recommended Dosage

- The recommended dosage of BIZENGRI is 750 mg as an intravenous (IV) infusion every 2 weeks until disease progression or unacceptable toxicity [see Dosage and Administration (2.7)].
- Administer premedications before each BIZENGRI infusion as recommended to reduce the risk of infusion-related reactions [see Dosage and Administration (2.4)].

2.4 Recommended Premedications

Prior to each infusion of BIZENGRI, administer premedications to reduce the risk of infusion-related reactions (IRRs) [see Warnings and Precautions (5.1)] (see Table 1).

Table 1: Premedications Prior to BIZENGRI Infusions
Medication | Dose | Route of Administration
Corticosteroid^1 | Dexamethasone (10 mg) | Oral or intravenous
Antipyretic | Acetaminophen (1,000 mg) | Oral or intravenous
H1 Antihistamine | Dexchlorpheniramine (5 mg) or other anti-H1 equivalent | Intravenous or oral
^1 Optional after initial BIZENGRI infusion

2.5 Dosage Modifications for Adverse Reactions

No dose reduction is recommended for BIZENGRI. The recommended dosage modifications of BIZENGRI for adverse reactions are provided in Table 2.

Table 2: Recommended BIZENGRI Dosage Modifications and Management for Adverse Reactions
Adverse Reaction | Severity | Dose Modifications and Management
Infusion-related reactions (IRRs)/Hypersensitivity/Anaphylactic Reactions [see Warnings and Precautions (5.1)] | ≤ Grade 3 IRR | - Interrupt BIZENGRI infusion if IRR is suspected and monitor patient until reaction symptoms resolve. - Provide symptomatic treatment as needed. - Resume the infusion at 50% of the infusion rate at which the reaction occurred. The infusion rate may be escalated if there are no additional symptoms. - Corticosteroid premedication can be used as necessary for subsequent BIZENGRI infusions [see Recommended Premedications (2.4)].
Infusion-related reactions (IRRs)/Hypersensitivity/Anaphylactic Reactions [see Warnings and Precautions (5.1)] | Grade 4 IRR or any grade hypersensitivity/ anaphylactic reaction | - Permanently discontinue BIZENGRI.
Interstitial Lung Disease (ILD)/Pneumonitis [see Warnings and Precautions (5.2)] | Grade 1 | - Interrupt BIZENGRI until recovery. - Consider prompt initiation of corticosteroids when the diagnosis is suspected. - Resume treatment after resolution.
Interstitial Lung Disease (ILD)/Pneumonitis [see Warnings and Precautions (5.2)] | ≥ Grade 2 | - Permanently discontinue BIZENGRI. - Promptly treat with corticosteroids.
Left Ventricular Dysfunction [see Warnings and Precautions (5.3)] | LVEF is 45-49% and absolute decrease from baseline ≥10% or LVEF less than 45% | - Interrupt BIZENGRI. - Repeat LVEF assessment within 3 weeks. - If LVEF is less than 45% or LVEF has not recovered to within 10% from baseline, permanently discontinue BIZENGRI. - If LVEF is 50% or greater or LVEF is 45-49% and recovered to within 10% of baseline, resume BIZENGRI and monitor LVEF every 12 weeks while on treatment and as clinically indicated.
Left Ventricular Dysfunction [see Warnings and Precautions (5.3)] | Symptomatic congestive heart failure (CHF) | - Permanently discontinue BIZENGRI.
Other Clinically Relevant Adverse Reactions [see Adverse Reactions (6.1)] | Grade 3 or 4 | - Withhold BIZENGRI until recovery to ≤ Grade 1 or baseline. - Provide symptomatic treatment as needed. - Resume treatment after resolution of symptoms.

2.6 Preparation

Dilute and prepare BIZENGRI for intravenous infusion before administration.

For the initial infusion, prepare BIZENGRI as close to administration time as possible to allow for the possibility of extended infusion time in the event of an infusion-related reaction.

- Check that the BIZENGRI solution is clear to slightly opalescent, colorless to slightly yellow. Parenteral drug products should be inspected visually for particulate matter and discoloration prior to administration, whenever solution and container permit. Do not use if discoloration or visible particles are present.
- Withdraw and then discard 37.5 mL 0.9% Sodium Chloride Injection from the 250 mL infusion bag. Only use infusion bags made of polyvinylchloride (PVC), polyolefin or polyolefin/polyamide coextruded plastic.
- Withdraw a total of 37.5 mL of BIZENGRI from 2 vials and add it to the infusion bag. The final volume in the infusion bag should be 250 mL. Discard any unused portion left in the vial.
- Gently invert the bag to mix the solution. Do not shake.
- If not used immediately, store the diluted solution refrigerated at 2°C to 8°C (36°F to 46°F) and protect from light after preparation unless the infusion is initiated within 2 hours of preparation.

2.7 Administration

- If the infusion time exceeds the recommended storage time, the infusion bag must be discarded and a new infusion bag prepared to continue the infusion. Diluted BIZENGRI solution must by administered within:
  - 6 hours from end of preparation of infusion solution stored at room temperature [15°C to 25°C (59°F to 77°F)]
  - 28 hours from end of preparation of infusion solution stored refrigerated [2°C to 8°C (36°F to 46°F)]
- If the diluted BIZENGRI solution has been refrigerated, allow it to reach room temperature (approximately 30 minutes) prior to administration.
- Administer diluted BIZENGRI solution [see Dosage and Administration (2.6)] by intravenous infusion using an infusion set made of either PVC, polyethylene (PE), polyurethane (PUR) or polybutadiene (PB) with an in-line, sterile, non-pyrogenic, low protein-binding polyethersulfone (PES) filter (pore size 0.2 micrometer).
- Do not infuse BIZENGRI concomitantly in the same IV line with other agents.
- Administer BIZENGRI infusion via a peripheral or central line.
- Monitor patients closely for signs and symptoms of infusion-related reactions during BIZENGRI infusion and monitor patients for at least 1 hour following completion of the first BIZENGRI infusion and as clinically indicated [see Warnings and Precautions (5.1)].
- Administer intravenous infusion over 4 hours.

3 DOSAGE FORMS AND STRENGTHS

Injection: 375 mg/18.75 mL (20 mg/mL) clear to slightly opalescent, colorless to slightly yellow solution in a single-dose vial.

4 CONTRAINDICATIONS

None.

5 WARNINGS AND PRECAUTIONS

5.1 Infusion-Related Reactions/Hypersensitivity/Anaphylactic Reactions

BIZENGRI can cause serious and life-threatening infusion-related reactions (IRRs), hypersensitivity and anaphylactic reactions. Signs and symptoms of IRR may include chills, nausea, fever, and cough.

In the eNRGy study, 13% of patients experienced IRRs, all were Grade 1 or 2; 91% occurred during the first infusion. The median time to onset was 63 minutes (range: 13 minutes to 240 minutes) from the start of infusion.

Administer BIZENGRI in a setting with emergency resuscitation equipment and staff who are trained to monitor for IRRs and to administer emergency medications. Monitor patients closely for signs and symptoms of infusion reactions during infusion and for at least 1 hour following completion of first BIZENGRI infusion and as clinically indicated. Prior to the first BIZENGRI infusion, premedicate with a corticosteroid, an H1 antihistamine and acetaminophen to reduce the risk of IRRs [see Dosage and Administration (2.4)]. Corticosteroid premedication can be used as necessary for subsequent BIZENGRI infusions.

Interrupt BIZENGRI infusion in patients with ≤ Grade 3 IRRs and administer symptomatic treatment as needed. Resume infusion at a reduced rate after resolution of symptoms [see Dosage and Administration (2.5)]. Immediately stop the infusion and permanently discontinue BIZENGRI for Grade 4 or life-threatening IRR or hypersensitivity/anaphylaxis reactions.

5.2 Interstitial Lung Disease/Pneumonitis

BIZENGRI can cause serious and life-threatening interstitial lung disease (ILD)/pneumonitis.

In the eNRGy study [see Adverse Reactions (6.1)], ILD/pneumonitis occurred in 2 (1.1%) patients treated with BIZENGRI. Grade 2 ILD/pneumonitis (Grade 2) resulting in permanent discontinuation of BIZENGRI occurred in 1 (0.6%) patient.

Monitor for new or worsening pulmonary symptoms indicative of ILD/pneumonitis (e.g., dyspnea, cough, fever). Immediately withhold BIZENGRI in patients with suspected ILD/pneumonitis and administer corticosteroids as clinically indicated. Permanently discontinue BIZENGRI if ILD/pneumonitis ≥ Grade 2 is confirmed [see Dosage and Administration (2.5)].

5.3 Left Ventricular Dysfunction

BIZENGRI can cause left ventricular dysfunction.

Left ventricular ejection fraction (LVEF) decrease occurred with anti-HER2 therapies, including BIZENGRI. Treatment with BIZENGRI has not been studied in patients with a history of clinically significant cardiac disease or LVEF less than 50% prior to initiation of treatment.

In the eNRGy study [see Adverse Reactions (6.1)], Grade 2 LVEF decrease [Grade 2 LVEF decrease (40%-50%; 10 - 19% drop from baseline)] occurred in 2% of evaluable patients. Cardiac failure without LVEF decrease occurred in 1.7% of patients including 1 (0.6%) fatal event.

Before initiating BIZENGRI, evaluate LVEF and monitor at regular intervals during treatment as clinically indicated. For LVEF of less than 45% or less than 50% with absolute decrease from baseline of 10% or greater is confirmed, permanently discontinue BIZENGRI. Permanently discontinue BIZENGRI in patients with symptomatic congestive heart failure (CHF) [see Dosage and Administration (2.5)].

5.4 Embryo-Fetal Toxicity

Based on its mechanism of action, BIZENGRI can cause fetal harm when administered to a pregnant woman. In literature reports, use of a HER2-directed antibody during pregnancy resulted in cases of oligohydramnios manifesting as fatal pulmonary hypoplasia, skeletal abnormalities, and neonatal death. Animal studies have demonstrated that inhibition of HER2 and/or HER3 results in impaired embryo-fetal development, including effects on cardiac, vascular and neuronal development, and embryolethality. Advise patients of the potential risk to a fetus. Verify the pregnancy status of females of reproductive potential prior to the initiation of BIZENGRI. Advise females of reproductive potential to use effective contraception during treatment with BIZENGRI and for 2 months after the last dose [see Use in Specific Populations (8.1, 8.3)].

6 ADVERSE REACTIONS

The following clinically significant adverse reactions are described elsewhere in the labeling:

- Infusion-Related Reactions/Hypersensitivity/Anaphylaxis [see Warnings and Precautions (5.1)]
- Interstitial Lung Disease/Pneumonitis [see Warnings and Precautions (5.2)]
- Left Ventricular Dysfunction [see Warnings and Precautions (5.3)]
- Embryo-Fetal Toxicity [see Warnings and Precautions (5.4)]

6.1 Clinical Trials Experience

Because clinical trials are conducted under widely varying conditions, adverse reaction rates observed in the clinical trials of a drug cannot be directly compared to rates in the clinical trials of another drug and may not reflect the rates observed in practice.

The pooled safety population described in the WARNINGS AND PRECAUTIONS reflects exposure to BIZENGRI as a single agent at 750 mg administered intravenously every 2 weeks until disease progression or unacceptable toxicity in 175 patients with NRG1 gene fusion positive tumors in the eNRGy study. Of these, there were 99 patients with NSCLC, 39 patients with pancreatic adenocarcinoma and 37 patients with other solid tumors [see Clinical Studies (14.1, 14.2)]. Among the 175 patients who received BIZENGRI, the median duration of exposure to BIZENGRI was 5.3 months (range: 0.1 to 36), including 45% of patients exposed for at least 6 months and 15% of patients exposed for at least 1 year. In this pooled safety population, the most common (≥ 10%) adverse reactions were diarrhea, musculoskeletal pain, fatigue, nausea, infusion-related reactions (IRR), dyspnea, rash, constipation, vomiting, abdominal pain, and edema. The most common Grade 3 or 4 laboratory abnormalities (≥ 2%) were increased GGT, decreased hemoglobin, decreased sodium, decreased platelets, increased AST, increased ALT, increased alkaline phosphatase, decreased magnesium, decreased phosphate, increased aPTT and increased bilirubin.

NRG1 Gene Fusion Positive Unresectable or Metastatic NSCLC

eNRGy Study

The safety of BIZENGRI was evaluated in the eNRGy study in 99 patients with unresectable or metastatic NSCLC with NRG1 gene fusions [see Clinical Studies (14.1)]. Patients received BIZENGRI as a single agent at 750 mg intravenously every 2 weeks until disease progression or unacceptable toxicity. Among patients who received BIZENGRI, 47% were exposed for 6 months or longer and 17% were exposed for greater than one year.

The median age was 66 years (range: 27 to 88), 54% were 65 years or older; 62% were female; 37% were White, 53% were Asian, 2% were Black or African American; and 1% were Hispanic or Latino.

Serious adverse reactions occurred in 25% of patients who received BIZENGRI. Serious adverse reactions in ≥ 2% of patients included pneumonia (n=4) dyspnea and fatigue (n=2 each). Serious adverse reactions occurring in one patient each were: abdominal pain, acute kidney injury, ascites, bradycardia, carotid artery stenosis, cellulitis, acute cholecystitis, COVID-19, decreased appetite, dehydration, dizziness, dysphagia, hyponatremia, ileus, lymphadenitis, nausea, gastric obstruction, pericardial effusion, pneumonitis, pulmonary hypertension, sepsis, staphylococcal infection, tumor pain, urinary tract infection, viral infection and vomiting. Fatal adverse reactions occurred in 3 (3%) patients and included respiratory failure (n=2) and cardiac failure (n=1).

Permanent discontinuation of BIZENGRI due to an adverse reaction occurred in 3% of patients. Adverse reactions resulting in permanent discontinuation of BIZENGRI included dyspnea, pneumonitis and sepsis (n=1 each).

Dosage interruptions of BIZENGRI due to an adverse reaction, excluding temporary interruptions of BIZENGRI due to infusion-related reactions, occurred in 29% of patients. Adverse reactions leading to dosage interruptions in ≥2% of patients included dyspnea, COVID-19, arrhythmia, increased ALT, increased AST, and pneumonia.

Table 3 summarizes the adverse reactions in the eNRGy study in patients with NRG1 gene fusion positive unresectable or metastatic NSCLC.

Table 3: Adverse Reactions (≥10%) in Patients with NRG1 Gene Fusion Positive NSCLC Who Received BIZENGRI in the eNRGy Study
Adverse Reaction^1 | BIZENGRI (N=99)
Adverse Reaction^1 | All Grades % | Grade 3 or 4 %
Gastrointestinal disorders
Diarrhea^2 | 25 | 2
Nausea | 10 | 1
Musculoskeletal and connective tissue disorders
Musculoskeletal pain^3 | 23 | 1
Respiratory, thoracic and mediastinal disorders
Dyspnea^4 | 18 | 5
Cough^5 | 15 | 1
General disorders and administration site conditions
Fatigue^6 | 17 | 2
Edema^7 | 11 | 0
Skin and subcutaneous tissue disorders
Rash^8 | 14 | 0
Injury, poisoning and procedural complications
Infusion-related reactions ^9 | 12 | 0
Metabolism and nutrition disorders
Decreased appetite | 11 | 1
^1 Based on NCI CTCAE v4.03 and MedDRA v26.0
^2 Includes post-procedural diarrhea
^3 Includes back pain, pain in extremity, musculoskeletal chest pain, myalgia, arthralgia, non-cardiac chest pain, bone pain, musculoskeletal stiffness, neck pain, spinal pain.
^4 Includes dyspnea exertional
^5 Includes productive cough
^6 Includes asthenia
^7 Includes breast edema, peripheral edema, face edema
^8 Includes eczema, erythema, dermatitis, dermatitis contact, rash maculopapular, rash erythematous.
^9 Includes chills, IRR, nausea, cough, diarrhea, back pain, body temperature increased, dyspnea, face edema, fatigue, non-cardiac chest pain, oropharyngeal discomfort, paresthesia, pyrexia, and vomiting. AEs that were considered IRRs were counted under the composite term ‘IRR’, irrespective of the reported PT.

Clinically relevant adverse reactions in <10% of patients receiving BIZENGRI were stomatitis (7%), vomiting (8%), cardiac failure and pneumonitis (2% each).

Table 4 summarizes the laboratory abnormalities in the eNRGy study in patients with NRG1 gene fusion positive unresectable or metastatic NSCLC.

Table 4: Select Laboratory Abnormalities ≥ 20% that Worsened from Baseline in Patients with NRG1 Gene Fusion Positive NSCLC Who Received BIZENGRI in the eNRGy Study
Laboratory Abnormality | BIZENGRI^1
Laboratory Abnormality | All Grades % | Grade 3 or 4 %
Hematology
Decreased hemoglobin | 35 | 4.2
Chemistry
Increased alanine aminotransferase | 30 | 3.1
Decreased magnesium | 28 | 4.3
Increased alkaline phosphatase | 27 | 0
Decreased phosphate | 26 | 1.1
Increased gamma-glutamyl transpeptidase | 23 | 5
Increased aspartate aminotransferase | 22 | 3.1
Decreased potassium | 21 | 2.1
^1 The denominator used to calculate the rate varied from 93 to 96 based on the number of patients with a baseline value and at least one post-treatment value.

NRG1 Gene Fusion Positive Unresectable or Metastatic Pancreatic Adenocarcinoma

eNRGy Study

The safety of BIZENGRI was evaluated in the eNRGy study in 39 patients with unresectable or metastatic pancreatic adenocarcinoma with NRG1 gene fusions [see Clinical Studies (14.2)]. Patients received BIZENGRI as a single agent at 750 mg intravenously every 2 weeks until disease progression or unacceptable toxicity. Among patients who received BIZENGRI, 50% were exposed for 6 months or longer and 13% were exposed for greater than one year.

The median age was 51 years (range: 21 to 74), 23% were 65 years or older; 49% were female; 82% were White, 13% were Asian, 2.6% were Black or African American; and 5% were Hispanic or Latino.

Serious adverse reactions occurred in 23% of patients who received BIZENGRI. Serious adverse reactions occurring in one patient each were: anemia, thrombocytopenia, tachycardia, abdominal pain, hemorrhoidal hemorrhage, nausea, cholestatic jaundice, COVID-19, liver abscess, traumatic fracture, blood creatinine increased, back pain, myelodysplastic syndrome, and respiratory disorder. There were 2 fatal adverse reactions, one due to COVID-19 and one due to respiratory failure.

Dosage interruptions of BIZENGRI due to an adverse reaction, excluding temporary interruptions of BIZENGRI due to infusion-related reactions, occurred in 33% of patients. Adverse reactions leading to dosage interruptions in ≥2% of patients included COVID-19, pneumonia, increased AST, neutropenia, abdominal pain, agitation, increased blood alkaline phosphatase, increased blood bilirubin, constipation, increased creatinine, hemorrhage, hyperbilirubinemia, cholestatic jaundice, tachycardia, traumatic fracture, and upper respiratory infection.

Table 5 summarizes the adverse reactions in the eNRGy study in patients with NRG1 gene fusion positive pancreatic adenocarcinoma.

Table 5: Adverse Reactions (≥10%) in Patients with NRG1 Gene Fusion Positive Pancreatic Adenocarcinoma Who Received BIZENGRI in the eNRGy Study
Adverse Reaction^1 | BIZENGRI (N=39)
Adverse Reaction^1 | All Grades (%) | Grade 3 or 4 (%)
Gastrointestinal disorders
Diarrhea | 36 | 5
Nausea | 23 | 5
Vomiting | 23 | 2.6
Abdominal pain | 18 | 5
Constipation | 15 | 0
Abdominal distension | 13 | 0
Stomatitis | 10 | 0
Musculoskeletal and connective tissue disorders
Musculoskeletal pain^2 | 28 | 2.6
General disorders and administration site conditions
Fatigue^3 | 21 | 5
Edema^4 | 13 | 0
Pyrexia | 10 | 0
Infections and infestations
COVID-19 | 18 | 0
Injury, poisoning and procedural complications
Infusion-related reactions^5 | 15 | 0
Vascular disorders
Hemorrhage^6 | 13 | 5
Psychiatric disorders
Anxiety | 10 | 0
Skin and subcutaneous tissue disorders
Dry skin | 10 | 0
^1 Based on NCI CTCAE v4.03 and MedDRA v26.0
^2 Includes back pain, pain in extremity, musculoskeletal chest pain, myalgia, arthralgia, non-cardiac chest pain, bone pain, musculoskeletal stiffness, neck pain, spinal pain
^3 Includes asthenia
^4 Includes peripheral edema, face edema, localized edema, peripheral swelling
^5 Includes chills, IRR, nausea, cough, diarrhea, back pain, body temperature increased, dyspnea, face edema, fatigue, non-cardiac chest pain, oropharyngeal discomfort, paresthesia, pyrexia, and vomiting
^6 Includes epistaxis, hematochezia, hematuria, hemorrhoidal hemorrhage

Clinically relevant adverse reactions in <10% of patients receiving BIZENGRI were decreased appetite (5%), and rash (8%) [including dermatitis acneiform, erythema, dermatitis, dermatitis contact, rash maculopapular, rash erythematous].

Table 6 summarizes the laboratory abnormalities in the eNRGy study in patients with NRG1 gene fusion positive pancreatic adenocarcinoma.

Table 6: Select Laboratory Abnormalities ≥ 20% That Worsened from Baseline in Patients with NRG1 Gene Fusion Positive Pancreatic Adenocarcinoma Who Received BIZENGRI in the eNRGy Study
Laboratory Abnormality | BIZENGRI^1 (N=39)
Laboratory Abnormality | All Grades (%) | Grade 3 or 4 (%)
Chemistry
Increased alanine aminotransferase | 51 | 5
Increased aspartate aminotransferase | 31 | 5
Increased bilirubin | 31 | 5
Decreased phosphate | 31 | 2.9
Increased alkaline phosphatase | 28 | 8
Decreased sodium | 28 | 10
Decreased albumin | 26 | 0
Decreased potassium | 26 | 2.6
Decreased magnesium | 24 | 2.6
Increased gamma-glutamyl transpeptidase | 23 | 15
Hematology
Decreased platelets | 26 | 10
Decreased hemoglobin | 23 | 10
Decreased leukocytes | 21 | 2.6
^1 The denominator used to calculate the rate varied from 35 to 39, based on the number of patients with a baseline value and at least one post-treatment value.

8 USE IN SPECIFIC POPULATIONS

8.1 Pregnancy

Risk Summary

Based on its mechanism of action, BIZENGRI can cause fetal harm when administered to a pregnant woman [see Clinical Pharmacology (12.1)]. There are no available data on the use of BIZENGRI in pregnant women to inform a drug-associated risk.

Animal studies have demonstrated that HER2 and/or HER3 deficiency results in embryo-fetal malformation, including effects on cardiac, vascular and neuronal development, and embryolethality (see Data).

Human IgG1 is known to cross the placenta; therefore, BIZENGRI has the potential to be transmitted from the mother to the developing fetus. Advise patients of the potential risk to a fetus.

There are clinical considerations if BIZENGRI is used in pregnant women, or if a patient becomes pregnant within 2 months after the last dose of BIZENGRI (see Clinical Considerations).

In the U.S. general population, the estimated background risk of major birth defects and miscarriage in clinically recognized pregnancies is 2% to 4% and 15% to 20%, respectively.

Clinical Considerations

Fetal/Neonatal Adverse Reactions

Monitor women who received BIZENGRI during pregnancy or within 2 months prior to conception for oligohydramnios. If oligohydramnios occurs, perform fetal testing that is appropriate for gestational age and consistent with community standards of care.

Data

Human Data

There are no available data on the use of BIZENGRI in pregnant women. In literature reports in pregnant women receiving a HER2-directed antibody, cases of oligohydramnios manifesting as fatal pulmonary hypoplasia, skeletal abnormalities, and neonatal death have been reported. These case reports described oligohydramnios in pregnant women who received HER2-directed antibody alone or in combination with chemotherapy. In some case reports, amniotic fluid index increased after use of a HER2-directed antibody was stopped.

Animal Data

There were no animal reproductive or developmental toxicity studies conducted with zenocutuzumab-zbco. A literature-based assessment of the effects on reproduction demonstrated that HER2 and HER3 are critically important in embryo-fetal development. HER2 knockout mice or mice expressing catalytically inactive HER2 die at mid-gestation due to cardiac dysfunction. HER2 knockout mice have also shown abnormal sympathetic nervous system development. In HER3-deficient mice, embryolethality occurred on embryonic day 13.5 due to cardiac and vascular defects, as well as abnormalities in other organs (neural crest, pancreas, stomach, and adrenal). In addition, HER3 is shown to be involved in mammary gland ductal morphogenesis in mice. Zenocutuzumab-zbco can cause embryo-fetal toxicity based on its mechanism of action.

8.2 Lactation

Risk Summary

There are no data on the presence of zenocutuzumab-zbco in human milk, the effects on the breastfed child, or the effects on milk production. Maternal IgG1 is known to be present in human milk. The effects of local gastrointestinal exposure and limited systemic exposure in the breastfed child to BIZENGRI are unknown. Consider the developmental and health benefits of breast feeding along with the mother's clinical need for BIZENGRI treatment and any potential adverse effects on the breastfed child from BIZENGRI or from the underlying maternal condition. This consideration should also take into account the elimination half-life of zenocutuzumab-zbco and washout period of 2 months.

8.3 Females and Males of Reproductive Potential

BIZENGRI can cause fetal harm when administered to a pregnant woman [see Use in Specific Populations (8.1)].

Pregnancy Testing

Verify the pregnancy status of females of reproductive potential prior to initiating BIZENGRI [see Use in Specific Populations (8.1)].

Contraception

Females

Advise female patients of reproductive potential to use effective contraception during treatment with BIZENGRI and for 2 months after the last dose.

8.4 Pediatric Use

The safety and effectiveness of BIZENGRI have not been established in pediatric patients.

8.5 Geriatric Use

Of the 175 patients with NRG1 gene fusion positive tumors in the eNRGy study treated with BIZENGRI at 750 mg every 2 weeks, 75 patients (43%) were 65 years of age or older and 26 patients (15%) were 75 years of age and older. No clinically important differences in safety or efficacy were observed between patients who were ≥65 years of age and younger patients.

11 DESCRIPTION

Zenocutuzumab-zbco is a low-fucose humanized full-length immunoglobulin G1 (IgG1) bispecific HER2- and HER3-directed antibody. It has a molecular weight of approximately 146 kDa and is produced in a mammalian cell line (Chinese Hamster Ovary [CHO]) using recombinant DNA technology.

BIZENGRI is a sterile, clear to slightly opalescent, colorless to slightly yellow, preservative-free injection for intravenous infusion in single-dose vials. The pH is 6.0. Each BIZENGRI vial contains 375 mg/18.75 mL zenocutuzumab-zbco at a concentration of 20 mg/mL. Each vial also contains the following inactive ingredients: histidine (34.9 mg), L-histidine hydrochloride monohydrate (51.1 mg), polysorbate 20 (3.7 mg), trehalose (1412 mg), and water for injection.

12 CLINICAL PHARMACOLOGY

12.1 Mechanism of Action

Zenocutuzumab-zbco is a bispecific antibody that binds to the extracellular domains of HER2 and HER3 expressed on the surface of cells, including tumor cells, inhibiting HER2:HER3 dimerization and preventing NRG1 binding to HER3. Zenocutuzumab-zbco decreased cell proliferation and signaling through the phosphoinositide 3-kinase (PI3K)-AKT-mammalian target of rapamycin (mTOR) pathway. In addition, zenocutuzumab-zbco mediates antibody-dependent cellular cytotoxicity (ADCC). Zenocutuzumab-zbco showed antitumor activity in mouse models of NRG1 fusion-positive lung and pancreatic cancers.

12.2 Pharmacodynamics

The exposure-response relationship and time-course of pharmacodynamic response for zenocutuzumab-zbco have not been fully characterized.

12.3 Pharmacokinetics

Zenocutuzumab-zbco pharmacokinetic parameters are expressed as mean unless otherwise specified. Zenocutuzumab-zbco exposure increases proportionally over a dose range from 480 mg (0.6 times the approved recommended dosage) to 900 mg (1.2 times the approved recommended dosage). The median time to steady state of zenocutuzumab-zbco concentrations is 8 weeks and the median accumulation ratio is 1.6-fold at the approved recommended dosage.

Distribution

Zenocutuzumab-zbco volume of distribution is 6 L (CV 18%).

Elimination

The steady state zenocutuzumab-zbco half-life is 8 days (SD ±1.3 days) with a clearance of 22 mL/h (CV 37%).

Metabolism

Zenocutuzumab-zbco is expected to be metabolized into small peptides by catabolic pathways.

Specific Populations

No clinically significant differences in the pharmacokinetics of zenocutuzumab-zbco were observed based on age (22 to 88 years), sex, race [White or Asian], body weight (38 to 126 kg), albumin level (20 to 49 g/L), mild or moderate renal impairment (creatinine clearance (CLcr) 30 to 89 mL/min), and mild hepatic impairment (total bilirubin >1 to 1.5 times ULN or AST > ULN).

The pharmacokinetics of zenocutuzumab-zbco in patients with moderate to severe hepatic impairment (total bilirubin > 1.5 to 3 times ULN with any AST) or severe renal impairment (CLcr < 30 mL/min) is unknown.

12.6 Immunogenicity

The observed incidence of anti-drug antibodies is highly dependent on the sensitivity and specificity of the assay. Differences in assay methods preclude meaningful comparison of the incidence of anti-drug antibodies in the studies below with the incidence of anti-drug antibodies in other studies, including those of BIZENGRI or of other zenocutuzumab products.

In patients who received BIZENGRI at the approved recommended dosage for up to 30 months, 7 of 153 (4.6%) patients developed anti-zenocutuzumab antibodies. Because of the low occurrence of anti-drug antibodies, the effect of these antibodies on the pharmacokinetics, pharmacodynamics, safety, and efficacy of zenocutuzumab is unknown.

13 NONCLINICAL TOXICOLOGY

13.1 Carcinogenesis, Mutagenesis, Impairment of Fertility

No studies have been performed to assess the carcinogenic or mutagenic potential of zenocutuzumab-zbco.

Animal fertility studies have not been conducted with zenocutuzumab-zbco.

14 CLINICAL STUDIES

14.1 Advanced Unresectable or Metastatic NRG1 Fusion-Positive Non-Small Cell Lung Cancer

The efficacy of BIZENGRI was evaluated in the eNRGy study (NCT02912949) a multicenter, open-label, multi-cohort clinical study. The study enrolled adult patients with advanced or metastatic NRG1 fusion-positive NSCLC who had disease progression following standard of care treatment for their disease. Identification of positive NRG1 gene fusion status was prospectively determined based on next generation sequencing (NGS) assays performed at local laboratories or central laboratories. Patients received BIZENGRI as an intravenous infusion, 750 mg every 2 weeks, until unacceptable toxicity or disease progression. Tumor assessments were performed every 8 weeks. The major efficacy outcome measures were confirmed overall response rate (ORR) and duration of response (DOR) as determined by blinded independent central review (BICR) according to Response Evaluation Criteria in Solid Tumors (RECIST v1.1). Efficacy was evaluated in 64 patients with NRG1 fusion-positive NSCLC previously treated with systemic therapy enrolled in eNRGy.

The trial population characteristics were: median age 63.5 years (range: 32 to 86) with 47% of patients ≥ 65 years of age; 64% female; 56% Asian, 33% White, and 11% other races or not reported; none were Hispanic or Latino; baseline ECOG performance status of 0 or 1 (97%) or 2 (3%) and 98% of patients had metastatic disease. Patients received a median of 2 prior systemic therapies (range 1 to 6); 95% had prior platinum chemotherapy and 64% had prior anti-PD-1/PD-L1 therapy. A total of 54 patients (84%) had an NRG1 gene fusion detected by RNA-based NGS that may include DNA sequencing and 9 (14%) had an NRG1 gene fusion detected by DNA-based NGS.

Efficacy results are summarized in Table 7 and Table 8.

Table 7: Efficacy Results for Advanced Unresectable or Metastatic NRG1 Fusion-Positive NSCLC in the eNRGy Study
Efficacy Parameter | BIZENGRI Previously Treated with Systemic Therapy (n = 64)
Overall response rate^1 (95% CI) | 33% (22%, 46%)
Complete response rate | 1.6%
Partial response rate | 31%
Duration of response
Median (95% CI) (months) | 7.4 (4.0, 16.6)
Patients with DOR ≥6 months^2 | 43%
^1 Confirmed overall response rate assessed by BICR
^2 Based on observed duration of response

Table 8: Efficacy Results by NRG1 Gene Fusion Partner in NRG1 Fusion-Positive NSCLC Patients in the eNRGy Study
NRG1 Partner^1 | BIZENGRI (n = 64) | ORR |  | DOR
NRG1 Partner^1 | BIZENGRI (n = 64) | n (%) | 95% CI | Range (Months)
CD74 | 37 | 12 (32) | (18, 50) | 1.8+; 20.3+
SLC3A2 | 14 | 5 (36) | (13, 65) | 3.6; 20.8+
SDC4 | 7 | 2 (29) | (3.7, 71) | 7.4; 16.6
CDH1 | 2 | 1 (50) | (1.3, 99) | 1.9+
FUT10 | 1 | PD | NA | NA
PVALB | 1 | PD | NA | NA
ST14 | 1 | PD | NA | NA
VAMP2 | 1 | PR | NA | 5.6
^1 Fusion partners identified in this primary analysis set (n=64) may not represent all potential fusion partners.
PR=partial response; PD=progressive disease; NA=not applicable; “+” indicates ongoing response-

14.2 Advanced Unresectable or Metastatic NRG1 Fusion-Positive Pancreatic Adenocarcinoma

The efficacy of BIZENGRI was evaluated in the eNRGy study (NCT02912949), a multicenter, open-label, multi-cohort clinical study. The study enrolled 30 adult patients with advanced or metastatic NRG1 fusion-positive pancreatic adenocarcinoma who had disease progression following standard of care treatment. Identification of an NRG1 gene fusion was prospectively determined in local laboratories using next generation sequencing (NGS). Patients received BIZENGRI as an intravenous infusion, 750 mg every 2 weeks, until unacceptable toxicity or disease progression. Tumor assessments were performed every 8 weeks. The major efficacy outcome measures were confirmed overall response rate (ORR) and duration of response (DOR) as determined by a blinded independent central review (BICR) according to Response Evaluation Criteria in Solid Tumors (RECIST) v1.1.

The trial population characteristics were: median age 49 years (range: 21 to 72) with 10% of patients ≥ 65 years of age; 43% female; 87% White, 7% Asian, 3.3% Black or African American, and 3.3% other races or not reported; 3.3% were Hispanic or Latino; baseline ECOG performance status of 0 (53%) or 1 (47%) and all patients had metastatic disease. Patients received a median of 2 prior systemic therapies (range 0 to 5); 97% had prior systemic therapy with FOLFIRINOX, gemcitabine/taxane-based therapy, or both. A total of 27 patients (90%) had an NRG1 gene fusion detected by RNA-based NGS that may include DNA sequencing and 3 (10%) had an NRG1 gene fusion detected by DNA-based NGS.

Efficacy results are summarized in Table 9 and Table 10.

Table 9: Efficacy Results for Advanced Unresectable or Metastatic NRG1 Fusion-Positive Pancreatic Adenocarcinoma in the eNRGy Study
Efficacy Parameter | BIZENGRI (n = 30)
Overall response rate^1 (95% CI) | 40% (23%, 59%)
Complete response rate | 3.3%
Partial response rate | 37%
Duration of response
Range (months) | 3.7, 16.6
Patients with DOR ≥6 months^2 | 67%
^1 Confirmed overall response rate assessed by BICR
^2 Based on observed duration of response

Table 10: Efficacy Results by NRG1 Gene Fusion Partner in NRG1 Fusion-Positive Pancreatic Adenocarcinoma Patients in the eNRGy Study
NRG1 Partner^1 | BIZENGRI (n = 30) | ORR |  | DOR
NRG1 Partner^1 | BIZENGRI (n = 30) | n (%) | 95% CI | Range (Months)
ATP1B1 | 14 | 7 (50) | (23, 77) | 3.7, 16.6
CD44 | 3 | 0 | (0, 71) | NA
NOTCH2 | 3 | 1 (33) | (0.8, 91) | 7.4+
SLC4A4 | 3 | 2 (67) | (9, 99) | 7.5+, 15.2+
AGRN | 1 | PR | NA | 9.1+
APP | 1 | PR | NA | 3.7
CDH1 | 2 | SD, SD | NA | NA
SDC4 | 1 | SD | NA | NA
THBS1 | 1 | PD | NA | NA
VTCN1 | 1 | SD | NA | NA
^1 Fusion partners identified in this primary analysis set (n=30) may not represent all potential fusion partners.
PR=partial response; PD=progressive disease; SD=stable disease; NA=not applicable; “+” indicates ongoing response

16 HOW SUPPLIED/STORAGE AND HANDLING

How Supplied

BIZENGRI (zenocutuzumab-zbco) injection is a sterile, clear to slightly opalescent, colorless to slightly yellow, preservative-free solution for intravenous infusion. Each single-dose vial contains 375 mg/18.75 mL (20 mg/mL) BIZENGRI. Two vials (equivalent to 1 dose) are packed in a single carton. (NDC 71837-1000-1 for individual vial and NDC 71837-1000-2 for a single carton).

Storage and Handling

Store in a refrigerator at 2°C to 8°C (36°F to 46°F) in original carton to protect from light. Do not freeze. Do not shake.

17 PATIENT COUNSELING INFORMATION

Advise the patient to read the FDA-approved patient labeling (Patient Information).

Infusion-Related Reactions/Hypersensitivity/Anaphylaxis

Advise patients that BIZENGRI can cause serious and life-threatening infusion-related reactions (IRRs). Advise patients to alert their healthcare provider immediately for any signs or symptoms of IRRs during and following the infusion [see Warnings and Precautions (5.1)].

Interstitial Lung Disease (ILD)/Pneumonitis

Inform patients that BIZENGRI can cause serious and life threatening ILD/pneumonitis. Advise patients to immediately contact their healthcare provider for new or worsening respiratory symptoms [see Warnings and Precautions (5.2)].

Left Ventricular Dysfunction

Inform patients that BIZENGRI can cause serious and life threatening left ventricular dysfunction. Advise patients to immediately contact their healthcare provider for new or worsening cardiovascular symptoms [see Warnings and Precautions (5.3)].

Embryo-Fetal Toxicity

- Inform female patients of the potential risk to a fetus. Advise female patients to contact their healthcare provider with a known or suspected pregnancy [see Warnings and Precautions (5.4), Use in Specific Populations (8.1)].
- Advise females of reproductive potential to use effective contraception during treatment with BIZENGRI and for 2 months after the last dose [see Use in Specific Populations (8.1, 8.3)].

Lactation

Advise women not to breastfeed during treatment with BIZENGRI and for 2 months after the last dose [see Use in Specific Populations (8.2)].

Manufactured by: Partner Therapeutics, Inc. Lexington, MA 02421

BIZENGRI® is a registered trademark of Merus N.V.

U.S. License Number 2087

©2025 Partner Therapeutics, Inc.

AW028-01

PATIENT INFORMATION
BIZENGRI® (bi zen gree)
(zenocutuzumab-zbco)
injection, for intravenous use

What is the most important information I should know about BIZENGRI?

BIZENGRI may cause serious side effects, including:

- Infusion-related, allergic and anaphylactic reactions. BIZENGRI may cause serious infusion-related and allergic reactions that can be life-threatening. Infusion-related reactions are also common during BIZENGRI treatment. Before each BIZENGRI infusion, your healthcare provider will give you medicines to help reduce your chance of getting infusion-related reactions. Your healthcare provider will monitor you for signs and symptoms during your infusion and for at least 1 hour after your first infusion and as needed. Tell your healthcare provider right away if you develop any of the following signs or symptoms during or after your BIZENGRI infusion:

- chills or shaking
- nausea, vomiting, or diarrhea
- fever
- cough
- sudden swelling of your face, tongue, throat, or troubled swallowing
- throat tightness or discomfort

- itching or rash
- shortness of breath or wheezing
- chest discomfort
- feeling light-headed
- dizziness
- back or neck pain
- feeling of numbness or tingling

- Lung problems. BIZENGRI may cause serious lung problems that may be life-threatening. If you develop lung problems, your healthcare provider may treat you with corticosteroid medicines. Tell your healthcare provider right away if you develop any new or worsening symptoms of lung problems, including:

- trouble breathing
- shortness of breath

- cough
- fever

- Heart problems that may affect your heart's ability to pump blood. BIZENGRI may cause serious and life-threatening heart problems that may lead to death. Your healthcare provider will check your heart function before you start treatment with BIZENGRI and as needed during your treatment. Tell your healthcare provider right away if you develop any new or worsening symptoms of heart problems, including:

- shortness of breath
- coughing
- tiredness
- swelling of your feet, ankles or legs

- irregular heartbeat
- sudden weight gain
- dizziness or feeling light-headed
- loss of consciousness

Your healthcare provider will check you for these side effects during your treatment with BIZENGRI and may delay your treatment, slow the infusion rate, or completely stop your treatment with BIZENGRI if you develop severe side effects.

- Harm to your unborn baby. Tell your healthcare provider right away if you become pregnant or think you might be pregnant during treatment with BIZENGRI.
  Females who are able to become pregnant:
  - Your healthcare provider will do a pregnancy test before you start treatment with BIZENGRI.
  - Use effective birth control (contraception) during treatment and for 2 months after your last dose of BIZENGRI.

See “What are the possible side effects of BIZENGRI?” for more information about side effects.

What is BIZENGRI?
BIZENGRI is a prescription medicine used to treat adults who have:

- lung cancer called non-small cell lung cancer (NSCLC):
  - that has a neuregulin 1 (NRG1) gene fusion and cannot be removed by surgery or has spread to other parts of the body (advanced unresectable or metastatic), and
  - whose disease has worsened on or after prior cancer treatment.
- pancreatic cancer called pancreatic adenocarcinoma:
  - that has a neuregulin 1 (NRG1) gene fusion and cannot be removed by surgery or has spread to other parts of the body (advanced unresectable or metastatic), and
  - whose disease has worsened on or after prior cancer treatment.

It is not known if BIZENGRI is safe and effective in children.

Before receiving BIZENGRI, tell your healthcare provider about all your medical conditions, including if you:

- have lung or breathing problems other than your lung cancer.
- have or have had any heart problems.
- are breastfeeding or plan to breastfeed. It is not known if BIZENGRI passes into your breast milk. Do not breastfeed during treatment and for 2 months after your last dose of BIZENGRI.

Tell your healthcare provider about all the medicines you take, including prescription and over-the counter medicines, vitamins, and herbal supplements.

How will I receive BIZENGRI?

- BIZENGRI will be given to you by your healthcare provider as an intravenous (IV) infusion into your vein, usually over 4 hours.
- BIZENGRI is usually given 1 time every 2 weeks.
- Your healthcare provider will decide how many treatments you will need.

What are the possible side effects of BIZENGRI?

BIZENGRI may cause serious side effects, including:

- See “What is the most important information I should know about BIZENGRI?”

The most common side effects of BIZENGRI include:

- diarrhea
- muscle or bone pain
- tiredness
- nausea
- shortness of breath

- rash
- constipation
- vomiting
- stomach-area (abdominal) pain
- swelling of your breast, face, ankles or legs

The most common severe abnormal blood test results with BIZENGRI include:

- increased blood levels of liver enzymes and bilirubin
- decreased red blood cell counts and platelet counts

- decreased blood level of sodium, magnesium, and phosphate
- increase in the time that it takes your blood to clot

These are not all of the possible side effects of BIZENGRI.
Call your doctor for medical advice about side effects. You may report side effects to FDA at 1-800-FDA-1088.

General information about safe and effective use of BIZENGRI:
Medicines are sometimes prescribed for purposes other than those listed in a Patient Information leaflet. You can ask your pharmacist or healthcare provider for information about BIZENGRI that is written for health professionals.

What are the ingredients in BIZENGRI?
Active ingredient: zenocutuzumab-zbco
Inactive ingredients: histidine, L-histidine hydrochloride monohydrate, polysorbate 20, trehalose, and water for injection
Manufactured by: Partner Therapeutics, Inc. Lexington, MA 02421
BIZENGRI® is a registered trademark of Merus N.V.
U.S. License Number 2087
© 2025 Partner Therapeutics, Inc.
For more information call 1-888-479-5385
AW029-01

This Patient Information has been approved by the U.S. Food and Drug Administration.

Issued: Mar/2025

Principal Display Panel – 750 mg Carton Label

NDC 71837-1000-2

Rx only

Bizengri®

zenocutuzumab-zbco
Injection 750 mg

375 mg/18.75 mL
(20 mg/mL) per vial

For Intravenous Infusion After Dilution

Each carton contains:

Two 375 mg/18.75 mL single-dose vials. Discard unused portion.

+ = one 750 mg dose

PTx

PARTNER
THERAPEUTICS